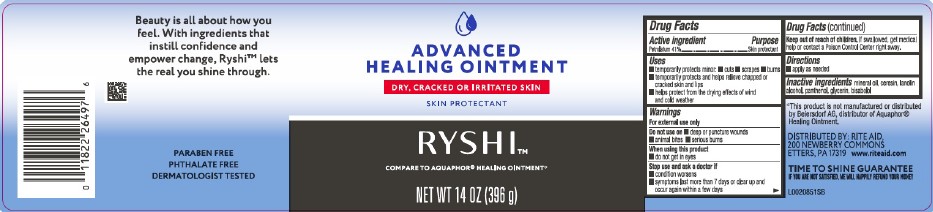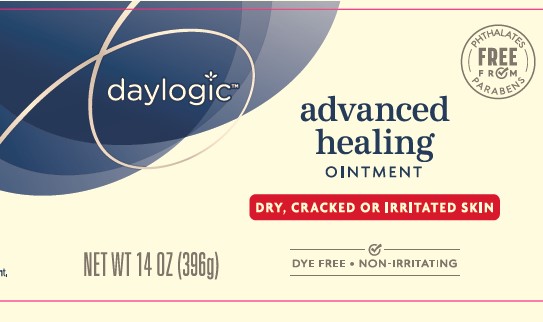 DRUG LABEL: Advanced Healing
NDC: 11822-1247 | Form: OINTMENT
Manufacturer: Rite Aid Corporation
Category: otc | Type: HUMAN OTC DRUG LABEL
Date: 20260130

ACTIVE INGREDIENTS: PETROLATUM 410 mg/1 g
INACTIVE INGREDIENTS: GLYCERIN; LEVOMENOL; MINERAL OIL; CERESIN; LANOLIN ALCOHOLS; PANTHENOL

RYSHI_Daylogic 247.000/247AA-AC
Healing Ointment for Dry and Cracked Skin

Active ingredient

Petrolaturm 41%

Purpose

Skin protectant

Uses

- temporarily protects minor: cuts, scrapes, burns
- temporarily protects and helps relieve chapped and cracked skin and lips
- helps protect from the drying effects of wind and cold weather

Warnings

For external use only

Do not use on

- deep or puncture wounds
- animal bites
- serious burns

When using this product

- do not get in eyes

Stop use and ask a doctor if

- condition worsens
- symptoms last more than 7 days or clear up and occur again within a few days

Keep out of reach of children.

If swallowed, get medical help or contract a Poison Control Center right away.

Directions

- apply as needed

Inactive ingredients

minerol oil, ceresin, lanolin alcohol, panthenol, glycerin, bisabolol

Disclaimer

*This product is not manufactured or distributed by Beiersdorf AG, distributor of Aquaphor® Healing Ointment.

Adverse reaction

DISTRIBUTED BY: RITE AID

200 NEWBERRY COMMONS

ETTERS, PA 17319 www.riteaid.com

TIME TO SHINE GUARANTEE

IF YOU ARE NOT SATISFIED, WE WILL HAPPILY REFUND YOUR MONEY

Claims

Beauty is all about how you feel. With ingredients that instill confidence and empower change, Ryshi™ lets the real you shince through.

PARABEN FREE

PHTHALATE FREE

DERMATOLOGIST TESTED

Principal display panel

daylogic

Free from

PHTHALATES

PARABEN

advanced

healing

OINTMENT

DRY, CRACKED OR IRRITATED SKIN

DYE FREE - NON-IRRITATING

NET WT 14 OZ (396g)

Principal display panel

ADVANCED HEALING OINTMENT

DRY, CRACKED OR IRRITATED SKIN

SKIN PROTECTANT

RYSHI™

COMPARE TO AQUAOHOR® HEALING OINTMENT*

NET WT 14 OZ (396 g)